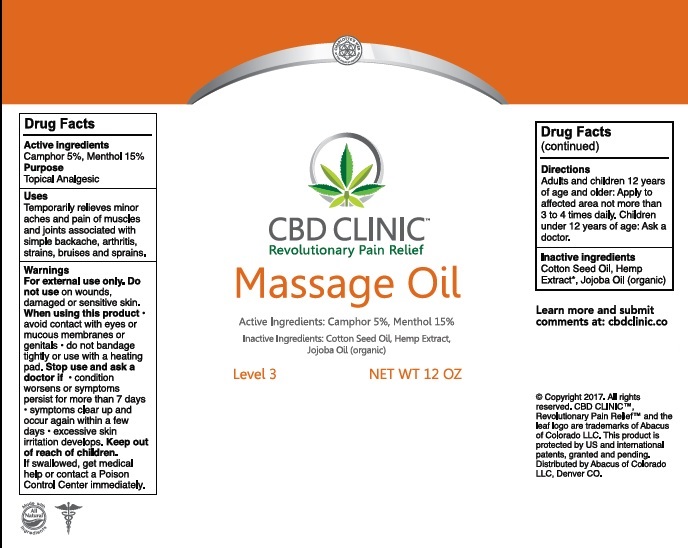 DRUG LABEL: CBD Clinic - Massage Oil - Level 3
NDC: 24909-713 | Form: OIL
Manufacturer: Aidance Skincare & Topical Solutions, LLC
Category: otc | Type: HUMAN OTC DRUG LABEL
Date: 20170515

ACTIVE INGREDIENTS: CAMPHOR (SYNTHETIC) 0.05 kg/1 kg; MENTHOL 0.15 kg/1 kg
INACTIVE INGREDIENTS: COTTONSEED OIL; HEMP; JOJOBA OIL

Drug Facts

Active Ingredients

Camphor 5%, Menthol 15%

Purpose

Camphor, Menthol - Topical Analgesics

Uses

Temporarily relieves minor aches and pains of muscles and joints associated with simple backache, arthritis, strains, bruises and sprains.

Warnings

For external use only. Do not use on wounds or damaged skin. When using this product - avoid contact with eyes or mucous membranes - do not bandage tightly or use with heating pad. Stop use and ask a doctor if - condition worsens or symptoms persist for more than 7 days - symptoms clear up and occur again within a few days - excessive skin irritation develops.

Keep out of reach of children.

If swallowed, get medical help or contact a Poison Control Center immediately.

Directions

Adults and children 12 years of age and older: Apply to affected area not more than 3 to 4 times daily. Children under 12 years of age: Ask a doctor.

Inactive Ingredients

Cotton Seed Oil, Hemp Extract, Jojoba Oil (organic)

PRINCIPAL DISPLAY PANEL - 12 Oz. Size

CBD CLINIC
Revolutionary Pain Relief
Massage Oil
Active Ingredients: Camphor 5%, Menthol 15%
Inactive Ingredients: Cotton Seed Oil, Hemp Extract, Jojoba Oil (organic)
Level 3 NET WT 12 OZ